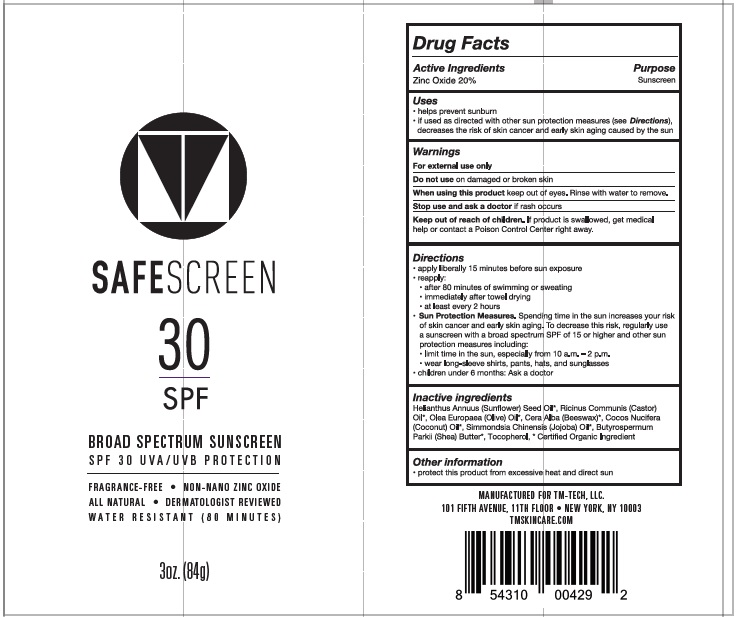 DRUG LABEL: SUNSCREEN
NDC: 62932-179 | Form: OINTMENT
Manufacturer: Private Label Select Ltd CO
Category: otc | Type: HUMAN OTC DRUG LABEL
Date: 20181118

ACTIVE INGREDIENTS: ZINC OXIDE 20 g/100 g
INACTIVE INGREDIENTS: HELIANTHUS ANNUUS SEED WAX; CASTOR OIL; OLEA EUROPAEA FRUIT VOLATILE OIL; YELLOW WAX; SIMMONDSIA CHINENSIS SEED WAX; SHEA BUTTER; TOCOPHEROL; COCONUT OIL

Safe Screen Sunscreen SPF30 84g